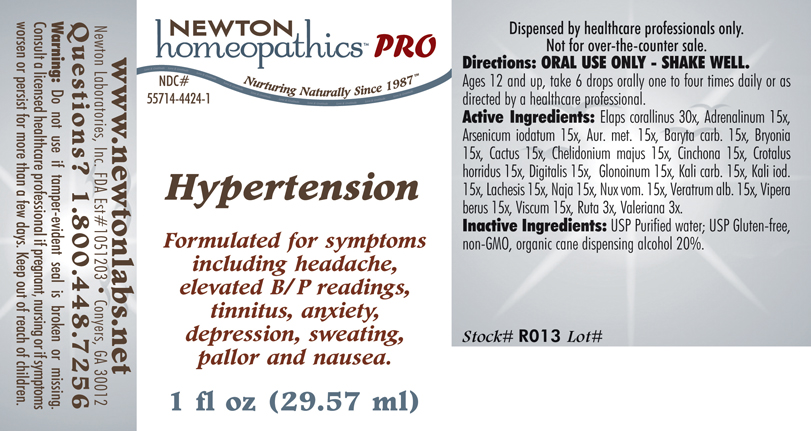 DRUG LABEL: Hypertension 
NDC: 55714-4424 | Form: LIQUID
Manufacturer: Newton Laboratories, Inc.
Category: homeopathic | Type: HUMAN PRESCRIPTION DRUG LABEL
Date: 20110601

ACTIVE INGREDIENTS: Micrurus Corallinus Venom 30 [hp_X]/1 mL; Epinephrine 15 [hp_X]/1 mL; Arsenic Triiodide 15 [hp_X]/1 mL; Gold 15 [hp_X]/1 mL; Barium Carbonate 15 [hp_X]/1 mL; Bryonia Alba Root 15 [hp_X]/1 mL; Selenicereus Grandiflorus Stem 15 [hp_X]/1 mL; Chelidonium Majus 15 [hp_X]/1 mL; Cinchona Officinalis Bark 15 [hp_X]/1 mL; Crotalus Horridus Horridus Venom 15 [hp_X]/1 mL; Digitalis 15 [hp_X]/1 mL; Nitroglycerin 15 [hp_X]/1 mL; Potassium Carbonate 15 [hp_X]/1 mL; Potassium Iodide 15 [hp_X]/1 mL; Lachesis Muta Venom 15 [hp_X]/1 mL; Naja Naja Venom 15 [hp_X]/1 mL; Strychnos Nux-vomica Seed 15 [hp_X]/1 mL; Veratrum Album Root 15 [hp_X]/1 mL; Vipera Berus Venom 15 [hp_X]/1 mL; Viscum Album Fruiting Top 15 [hp_X]/1 mL; Ruta Graveolens Flowering Top 3 [hp_X]/1 mL; Valerian 3 [hp_X]/1 mL
INACTIVE INGREDIENTS: Alcohol

Hypertension

PRODUCT NAME & INDICATIONS SECTION

HYPERTENSION Formulated for symptoms including headache, elevated B/P readings, tinnitus, anxiety, depression, sweating, pallor and nausea.

DIRECTION SECTION

Directions: ORAL USE ONLY - SHAKE WELL. Ages 12 and up, take 6 drops orally one to four times daily or as directed by a healthcare professional.

ACTIVE INGREDIENT SECTION

Elaps corallinus 30x, Adrenalinum 15x, Arsenicum iodatum 15x, Aur. met. 15x, Baryta carb. 15x, Bryonia 15x, Cactus 15x, Chelidonium majus 15x, Cinchona 15x, Crotalus horridus 15x, Digitalis 15x, Glonoinum 15x, Kali carb. 15x, Kali iod. 15x, Lachesis 15x, Naja 15x, Nux vom. 15x, Veratrum alb. 15x, Vipera berus 15x, Viscum 15x, Ruta 3x, Valeriana 3x.

PURPOSE SECTION

Formulated for symptoms including headache, elevated B/P readings, tinnitus, anxiety, depression, sweating, pallor and nausea.

INACTIVE INGREDIENT SECTION

Inactive Ingredients:USP Purified Water; USP Gluten-free, non-GMO, organic cane dispensing alcohol 20%.

QUESTIONS? SECTION

www.newtonlabs.net Newton Laboratories, Inc. FDA Est # 1051203 - Conyers, GA 30012
Questions? 1.800.448.7256

WARNINGS SECTION

Warning: Do not use if tamper - evident seal is broken or missing. Consult a licensed healthcare professional if pregnant, nursing or if symptoms worsen or persist for more than a few days. Keep out of reach of children.

OTC - PREGNANCY OR BREAST FEEDING SECTION

Consult a licensed healthcare professional if pregnant or nursing or if symptoms worsen or persist for more than a few days.

OTC - KEEP OUT OF REACH OF CHILDREN SECTION

Keep out of reach of children.